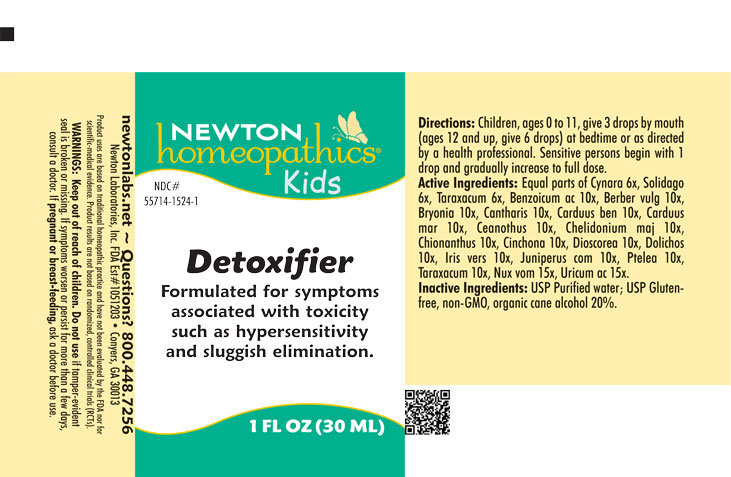 DRUG LABEL: Detoxifier
NDC: 55714-1524 | Form: LIQUID
Manufacturer: Newton Laboratories, Inc.
Category: homeopathic | Type: HUMAN OTC DRUG LABEL
Date: 20250723

ACTIVE INGREDIENTS: CYNARA SCOLYMUS LEAF 6 [hp_X]/1 mL; DIOSCOREA VILLOSA TUBER 10 [hp_X]/1 mL; BENZOIC ACID 10 [hp_X]/1 mL; BERBERIS VULGARIS ROOT BARK 10 [hp_X]/1 mL; BRYONIA ALBA ROOT 10 [hp_X]/1 mL; LYTTA VESICATORIA 10 [hp_X]/1 mL; CENTAUREA BENEDICTA 10 [hp_X]/1 mL; MILK THISTLE 10 [hp_X]/1 mL; CEANOTHUS AMERICANUS LEAF 10 [hp_X]/1 mL; CHELIDONIUM MAJUS 10 [hp_X]/1 mL; CHIONANTHUS VIRGINICUS BARK 10 [hp_X]/1 mL; CINCHONA OFFICINALIS BARK 10 [hp_X]/1 mL; IRIS VERSICOLOR ROOT 10 [hp_X]/1 mL; JUNIPER BERRY 10 [hp_X]/1 mL; PTELEA TRIFOLIATA BARK 10 [hp_X]/1 mL; MUCUNA PRURIENS FRUIT TRICHOME 10 [hp_X]/1 mL; TARAXACUM OFFICINALE 10 [hp_X]/1 mL; STRYCHNOS NUX-VOMICA SEED 15 [hp_X]/1 mL; URIC ACID 15 [hp_X]/1 mL; SOLIDAGO VIRGAUREA FLOWERING TOP 6 [hp_X]/1 mL
INACTIVE INGREDIENTS: ALCOHOL; WATER

Detox 1524L

INDICATIONS & USAGE SECTION

Formulated for symptoms associated with toxicity such as hypersensitivity and sluggish elimination.

OTC - ACTIVE INGREDIENT SECTION

Equal parts of Cynara scolymus 6x, Solidago virgaurea 6x, Taraxacum officinale 6x, Benzoicum acidum 10x, Berberis vulgaris 10x, Bryonia 10x, Cantharis 10x, Carduus benedictus 10x, Carduus marianus 10x,Ceanothus americanus 10x, Chelidonium majus 10x, Chionanthus virginica 10x, Cinchona officinalis 10x, Dioscorea villosa 10x, Dolichos pruriens 10x, Iris versicolor 10x, Juniperus communis 10x, Ptelea trifoliata 10x, Taraxacum officinale 10x, Nux vomica 15x, Uricum acidum 15x.

OTC - PURPOSE SECTION

Formulated for symptoms associated with toxicity such as hypersensitivity, sluggish elimination and other related symptoms.

INACTIVE INGREDIENT SECTION

USP Purified Water; USP Gluten-free, non-GMO, organic cane alcohol 20%.

QUESTIONS SECTION

newtonlabs.net – Questions? 800.448.7256

Newton Laboratories, Inc. FDA Est # 1051203 - Conyers, GA 30013

WARNINGS SECTION

WARNINGS: Keep out of reach of children. Do not use if tamper-evident seal is broken or missing. If symptoms worsen or persist for more than a few days, consult a doctor. If pregnant or breast-feeding, ask a doctor before use.

OTC - PREGNANCY OR BREAST FEEDING SECTION

If pregnant or breast-feeding, ask a doctor before use.

OTC - KEEP OUT OF REACH OF CHILDREN SECTION

Keep out of reach of children.

DOSAGE & ADMINISTRATION SECTION

Directions: Children, ages 0 to 11, give 3 drops by mouth (ages 12 and up, give 6 drops) at bedtime or as directed by a health professioal. Sensitive person begin with 1 drop and gradually increase to full dose.